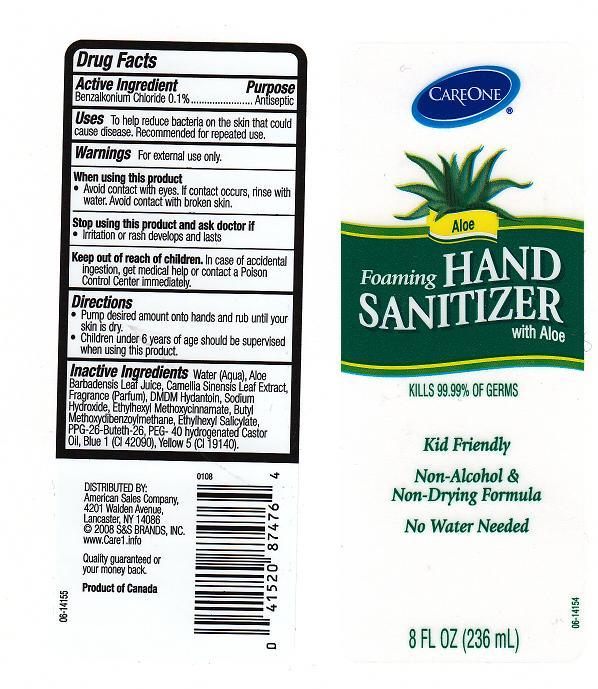 DRUG LABEL: FOAMING HAND SANITIZER
NDC: 41520-240 | Form: GEL
Manufacturer: AMERICAN SALES COMPANY
Category: otc | Type: HUMAN OTC DRUG LABEL
Date: 20111006

ACTIVE INGREDIENTS: BENZALKONIUM CHLORIDE 0.1 mL/100 mL
INACTIVE INGREDIENTS: WATER; ALOE VERA LEAF; GREEN TEA LEAF; DMDM HYDANTOIN; SODIUM HYDROXIDE; OCTINOXATE; AVOBENZONE; OCTISALATE; POLYOXYL 40 HYDROGENATED CASTOR OIL; FD&C BLUE NO. 1; FD&C YELLOW NO. 5

DRUG FACTS

ACTIVE INGREDIENT

BENZALKONIUM CHLORIDE 0.1%

PURPOSE

ANTISEPTIC

USES

TO HELP REDUCE BACTERIA ON THE SKIN THAT COULD CAUSE DISEASE. RECOMMENDED FOR REPEAT USE.

WARNINGS

FOR EXTERNAL USE ONLY.

WHEN USING THIS PRODUCT

AVOID CONTACT WITH EYES. IF CONTACT OCCURS, RINSE WITH WATER. AVOID CONTACT WITH BROKEN SKIN.

STOP USING THIS PRODUCT AND ASK DOCTOR IF

IRRITATION OR RASH DEVELOPS AND LASTS.

KEEP OUT OF REACH OF CHILDREN

IN CASE OF ACCIDENTAL INGESTION, GET MEDICAL HELP OR CONTACT A POISON CONTROL CENTER IMMEDIATELY.

DIRECTIONS

- PUMP DESIRED AMOUNT ONTO HANDS AND RUB UNTIL YOUR SKIN IS DRY.
- CHILDREN UNDER 6 YEARS OF AGE SHOULD BE SUPERVISED WHEN USING THIS PRODUCT.

INACTIVE INGREDIENTS

WATER, ALOE BARBADENSIS LEAF JUICE, CAMELLIA SINENSIS LEAF EXTRACT, FRAGRANCE, DMDM HYDANTOIN, SODIUM HYDROXIDE, ETHYLHEXYL METHOXYCINNAMATE, BUTYL METHOXYDIBENZOYLMETHANE, ETHYLHEXYL SALICYLATE, PPG-26-BUTETH-26, PEG-40 HYDROGENATED CASTOR OIL, BLUE 1 (CI 42090), YELLOW 5 (CI 19140).